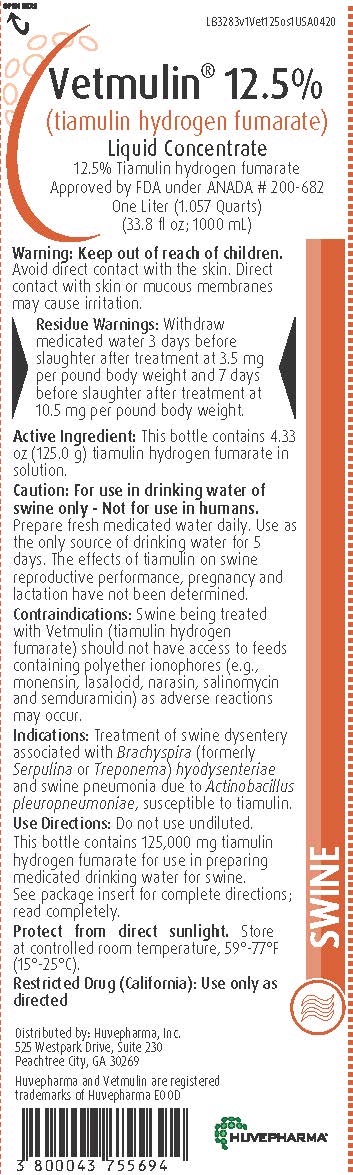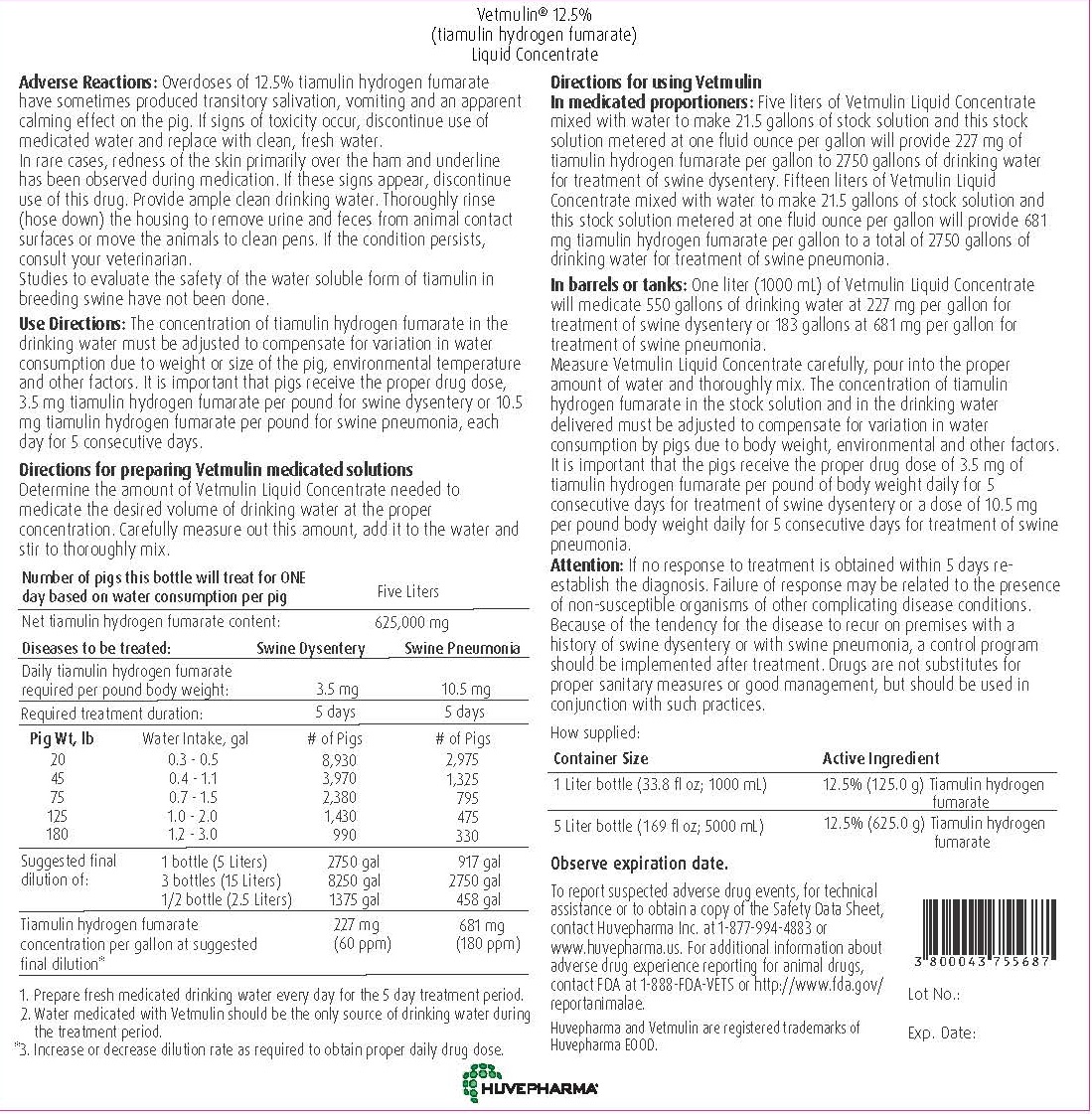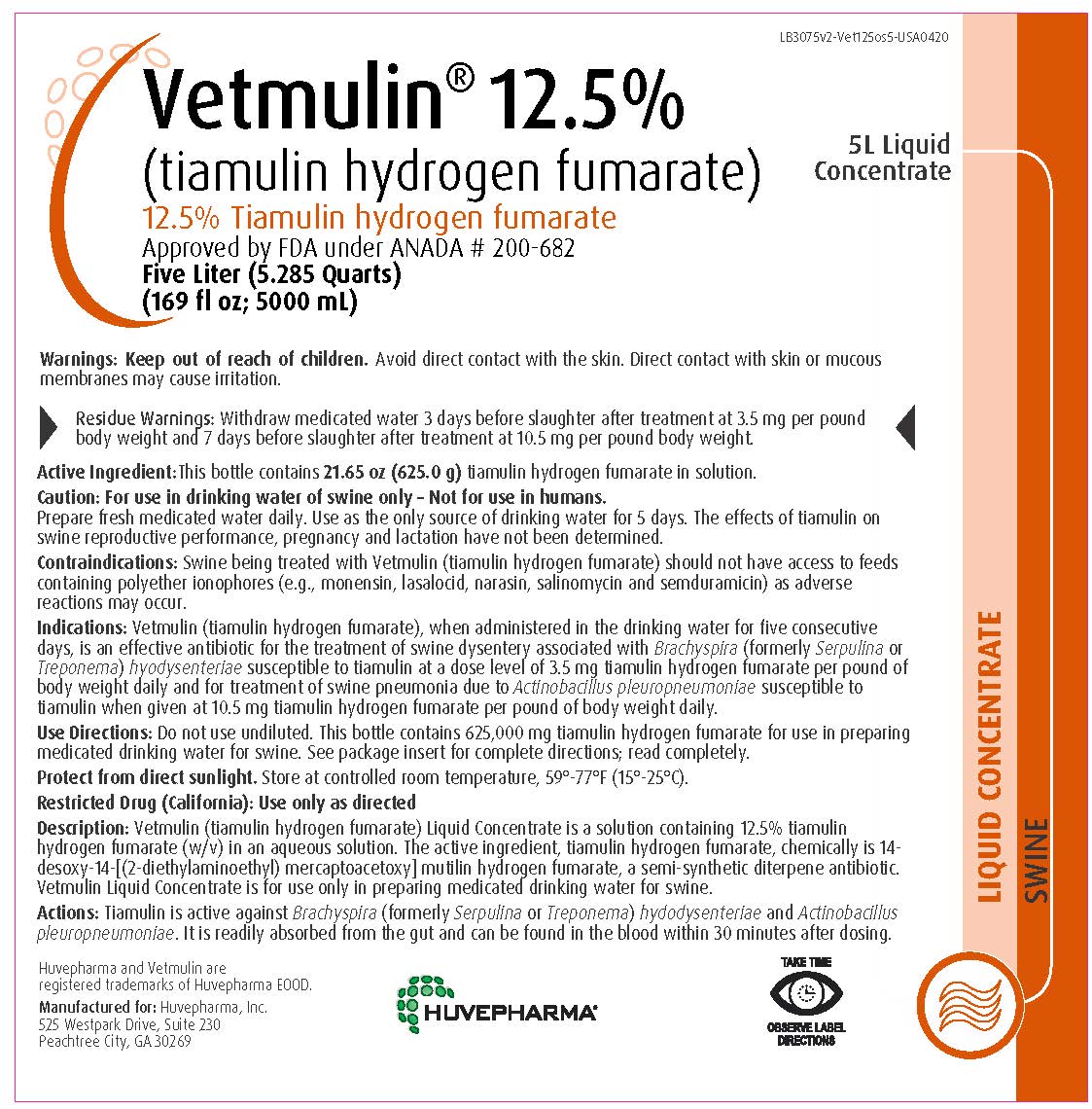 DRUG LABEL: Vetmulin
NDC: 23243-0073 | Form: CONCENTRATE
Manufacturer: Huvepharma, Inc
Category: animal | Type: OTC ANIMAL DRUG LABEL
Date: 20230824

ACTIVE INGREDIENTS: tiamulin fumarate 0.125 g/1 mL

Vetmulin® 12.5%
(tiamulin hydrogen fumarate)

Liquid Concentrate

WARNINGS

Warning: Keep out of reach of children.
Avoid direct contact with the skin. Direct contact with skin or mucous membranes may cause irritation.

RESIDUE WARNING

Residue Warnings: Withdraw medicated water 3 days before slaughter after treatment at 3.5 mg per pound body weight and 7 days before slaughter after treatment at 10.5 mg per pound body weight.

Active Ingredient: This bottle contains 4.33 oz (125.0 g) tiamulin hydrogen fumarate in
solution.

GENERAL PRECAUTIONS

Caution: For use in drinking water of swine only - Not for use in humans.
Prepare fresh medicated water daily. Use as the only source of drinking
water for 5 days. The effects of tiamulin on swine reproductive performance,
pregnancy and lactation have not been determined.

CONTRAINDICATIONS

Contraindications: Swine being treated with Vetmulin (tiamulin hydrogen
fumarate) should not have access to feeds containing polyether ionophores (e.g.,
monensin, lasalocid, narasin, salinomycin and semduramicin) as adverse reactions
may occur.

INDICATIONS AND USAGE

Indications: Treatment of swine dysentery associated with Brachyspira (formerly
Serpulina or Treponema) hyodysenteriae and swine pneumonia due to Actinobacillus
pleuropneumoniae, susceptible to tiamulin.

USER SAFETY WARNINGS

Use Directions: Do not use undiluted. This bottle contains 125,000 mg tiamulin
hydrogen fumarate for use in preparing medicated drinking water for swine.
See package insert for complete directions; read completely.

STORAGE AND HANDLING

Protect from direct sunlight. Store at controlled room temperature, 59°-77°F
(15°-25°C).
Restricted Drug (California): Use only as directed

Distributed by: Huvepharma, Inc.
525 Westpark Drive, Suite 230
Peachtree City, GA 30269

Huvepharma and Vetmulin are registered
trademarks of Huvepharma EOOD

DESCRIPTION

Description: Vetmulin (tiamulin hydrogen fumarate) Liquid Concentrate is a solution
containing 12.5% tiamulin hydrogen fumarate (w/ v) in an aqueous solution.

The active ingredient, tiamulin hydrogen fumarate, chemically is 14-desoxy-14-[(2-diethylaminoethyl)
mercaptoacetoxy] mutilin hydrogen fumarate, a semi-synthetic diterpene antibiotic. Vetmulin
Liquid Concentrate is for use only in preparing medicated drinking water for swine.

MECHANISM OF ACTION

Actions: Tiamulin is active against Brachyspira (formerly Serpulina or Treponema) hyodysenteriae
and Actinobacillus pleuropneumoniae. It is readily absorbed from the gut and can be found in the
blood within 30 minutes after dosing.

VETERINARY INDICATIONS

Indications: Vetmulin (tiamulin hydrogen fumarate), when administered in the drinking
water for five consecutive days, is an effective antibiotic for the treatment of swine dysentery
associated with Brachyspira (formerly Serpulina or Treponema) hyodysenteriae susceptible to
tiamulin at a dose level of 3.5 mg tiamulin hydrogen fumarate per pound of body weight
daily and for treatment of swine pneumonia due to Actinobacillus pleuropneumoniae susceptible to
tiamulin when given at 10.5 mg tiamulin hydrogen fumarate per pound of body weight daily.

CONTRAINDICATIONS

Contraindications: Swine being treated with Vetmulin (tiamulin hydrogen fumarate) should not
have access to feeds containing polyether ionophores (e.g., monensin, lasalocid, narasin,
salinomycin and semduramicin) as adverse reactions may occur.

WARNINGS

Warning: Keep out of reach of children. Avoid contact with skin. Direct contact with skin or
mucous membranes may cause irritation.

RESIDUE WARNING

Residue Warnings: Withdraw medicated water 3 days before slaughter after treatment
at 3.5 mg per pound body weight and 7 days before slaughter after treatment at 10.5 mg
per pound body weight.

GENERAL PRECAUTIONS

Caution: For use in drinking water of swine only - Not for use in humans.
Prepare fresh medicated water daily. The effects of tiamulin on swine reproductive performance,
pregnancy and lactation have not been determined.

ADVERSE REACTIONS

Adverse Reactions: Overdoses of 12.5% tiamulin hydrogen fumarate have sometimes produced
transitory salivation, vomiting and an apparent calming effect on the pig. If signs of toxicity occur,
discontinue use of medicated water and replace with clean, fresh water.

In rare cases, redness of the skin primarily over the ham and underline has been observed during
medication. If these signs appear, discontinue use of this drug. Provide ample clean drinking water.
Thoroughly rinse (hose down) the housing to remove urine and feces from animal contact
surfaces or move the animals to clean pens. If the condition persists, consult your veterinarian.

Studies to evaluate the safety of the water soluble form of tiamulin in breeding swine have
not been done.

DOSAGE AND ADMINISTRATION

Use Directions: The concentration of tiamulin hydrogen fumarate in the drinking water must be
adjusted to compensate for variation in water consumption due to weight or size of the pig,
environmental temperature and other factors. It is important that pigs receive the proper drug dose,
3.5 mg tiamulin hydrogen fumarate per pound for swine dysentery or 10.5 mg tiamulin hydrogen
fumarate per pound for swine pneumonia, each day for 5 consecutive days.

VETERINARY INDICATIONS

Directions for preparing Vetmulin medicated solutions

Determine the amount of Vetmulin Liquid Concentrate needed to medicate the desired volume of drinking water at the proper concentration.
Carefully measure out this amount, add it to the water and stir to thoroughly mix.

Number of pigs this bottle will treat for ONE day based on water consumption per pig |  | One Liter
Net tiamulin hydrogen fumarate content: |  | 125,000 mg
Diseases to be treated: |  | Swine Dysentery | Swine Pneumonia
Daily tiamulin hydrogen fumarate required per pound body weight: |  | 3.5 mg | 10.5 mg
Required treatment duration: |  | 5 days | 5 days
Pig Wt, lb | Water Intake, gal | # of Pigs | # of Pigs
20 | 0.3 - 0.5 | 1,786 | 595
45 | 0.4 - 1.1 | 794 | 265
75 | 0.7 - 1.5 | 476 | 159
125 | 1.0 - 2.0 | 286 | 95
180 | 1.2 - 3.0 | 198 | 66
Suggested final dilution of: | 1 bottle (1 Liter) | 550 gal | 183 gal
Suggested final dilution of: | 3 bottles (3 Liters) | 1650 gal | 550 gal
Suggested final dilution of: | 1/2 bottle (0.5 Liters) | 275 gal | 92 gal
Tiamulin hydrogen fumarate concentration per gallon at suggested final dilution* |  | 227 mg | 681 mg
Tiamulin hydrogen fumarate concentration per gallon at suggested final dilution* |  | (60 ppm) | (180 ppm)
1. Prepare fresh medicated drinking water every day for the 5 day treatment period.
2. Water medicated with Vetmulin should be the only source of drinking water during the treatment period.
*3. Increase or decrease dilution rate as required to obtain proper daily drug dose.

VETERINARY INDICATIONS

Directions for using Vetmulin

In medicated proportioners: One liter of Vetmulin Liquid Concentrate mixed with water to make 4.3 gallons of stock solution and this stock solution metered at one fluid ounce per gallon will provide 227 mg of tiamulin hydrogen fumarate per gallon to 550 gallons of drinking water for treatment of swine dysentery. Three liters of Vetmulin Liquid Concentrate mixed with water to make 4.3 gallons of stock solution and this stock solution metered at one fluid ounce per gallon will provide 681 mg tiamulin hydrogen fumarate per gallon to a total of 550 gallons of drinking water for treatment of swine pneumonia.

In barrels or tanks: One liter (1000 mL) of Vetmulin Liquid Concentrate will medicate 550 gallons of drinking water at 227 mg per gallon for
treatment of swine dysentery or 183 gallons at 681 mg per gallon for treatment of swine pneumonia.

Measure Vetmulin Liquid Concentrate carefully, pour into the proper amount of water and thoroughly mix. The concentration of tiamulin
hydrogen fumarate in the stock solution and in the drinking water delivered must be adjusted to compensate for variation in water consumption
by pigs due to body weight, environmental and other factors. It is important that the pigs receive the proper drug dose of 3.5 mg of tiamulin
hydrogen fumarate per pound of body weight daily for 5 consecutive days for treatment of swine dysentery or a dose of 10.5 mg per pound
body weight daily for 5 consecutive days for treatment of swine pneumonia.

Attention: If no response to treatment is obtained within 5 days re-establish the diagnosis. Failure of response may be related to the
presence of non-susceptible organisms of other complicating disease conditions. Because of the tendency for the disease to recur on premises
with a history of swine dysentery or with swine pneumonia, a control program should be implemented after treatment. Drugs are not
substitutes for proper sanitary measures or good management, but should be used in conjunction with such practices.

How supplied:

Container Size | Active Ingredients
1 Liter bottle | 12.5% (125.0 g)
(33.8 fl oz; 1000 mL) | Tiamulin hydrogen fumarate
5 Liter bottle | 12.5% (625.0 g)
(169 fl oz; 5000 mL) | Tiamulin hydrogen fumarate
Protect from direct sunlight. Store at controlled room temperature, 59°–77°F (15°–25°C).

Observe expiration date.

ADVERSE REACTIONS

To report suspected adverse drug events, for technical assistance or to obtain a copy of the
Safety Data Sheet, contact Huvepharma Inc. at 1-877-994-4883 or www.huvepharma.us. For
additional information about adverse drug experience reporting for animal drugs, contact
FDA at 1-888-FDA-VETS or http://www.fda.gov/ reportanimalae.

Principal Display Panel - Vetmulin 1000 mL Bottle Label

Vetmulin® 12.5%

(tiamulin hydrogen fumarate)

Liquid Concentrate

12.5% Tiamulin hydrogen fumarate

Approved by FDA under ANADA # 200-682

One Liter (1.057 Quarts)

(33.8 fl oz; 1000 mL)

Principal Display Panel - Vetmulin 5000 mL Bottle Label

Vetmulin® 12.5%

(tiamulin hydrogen fumarate)

Liquid Concentrate

12.5% Tiamulin hydrogen fumarate

Approved by FDA under ANADA # 200-682

Five Liter (5.285 Quarts)

(169 fl oz; 5000 mL)